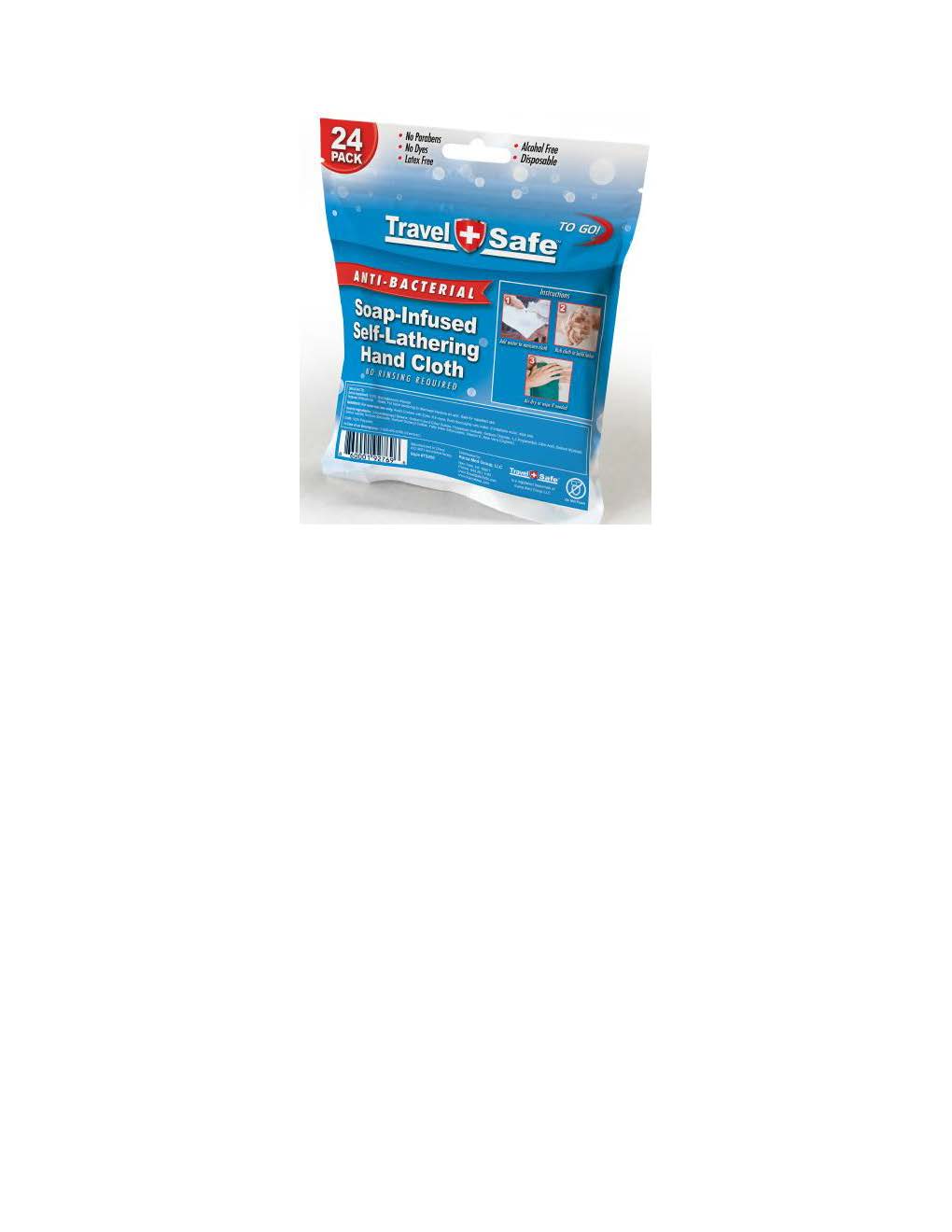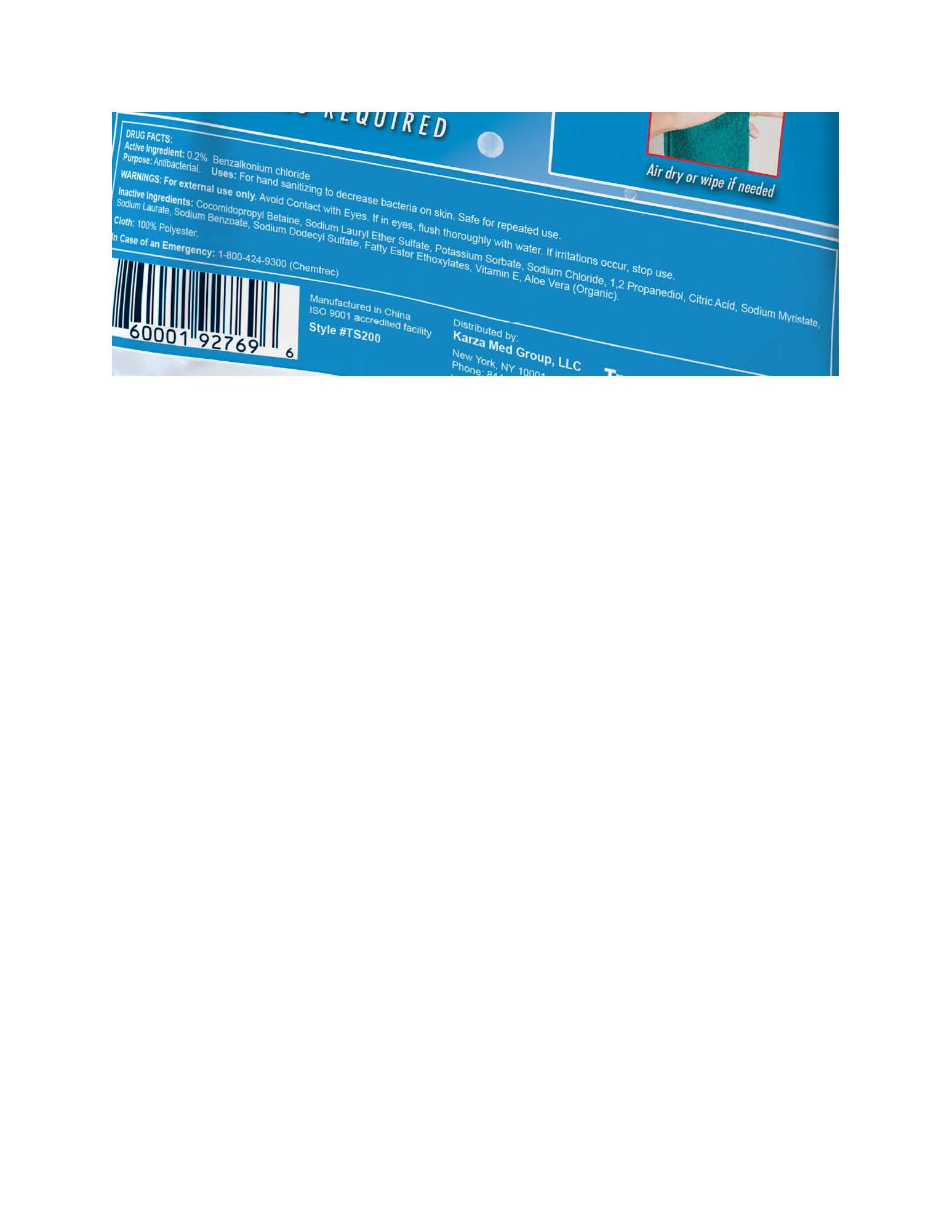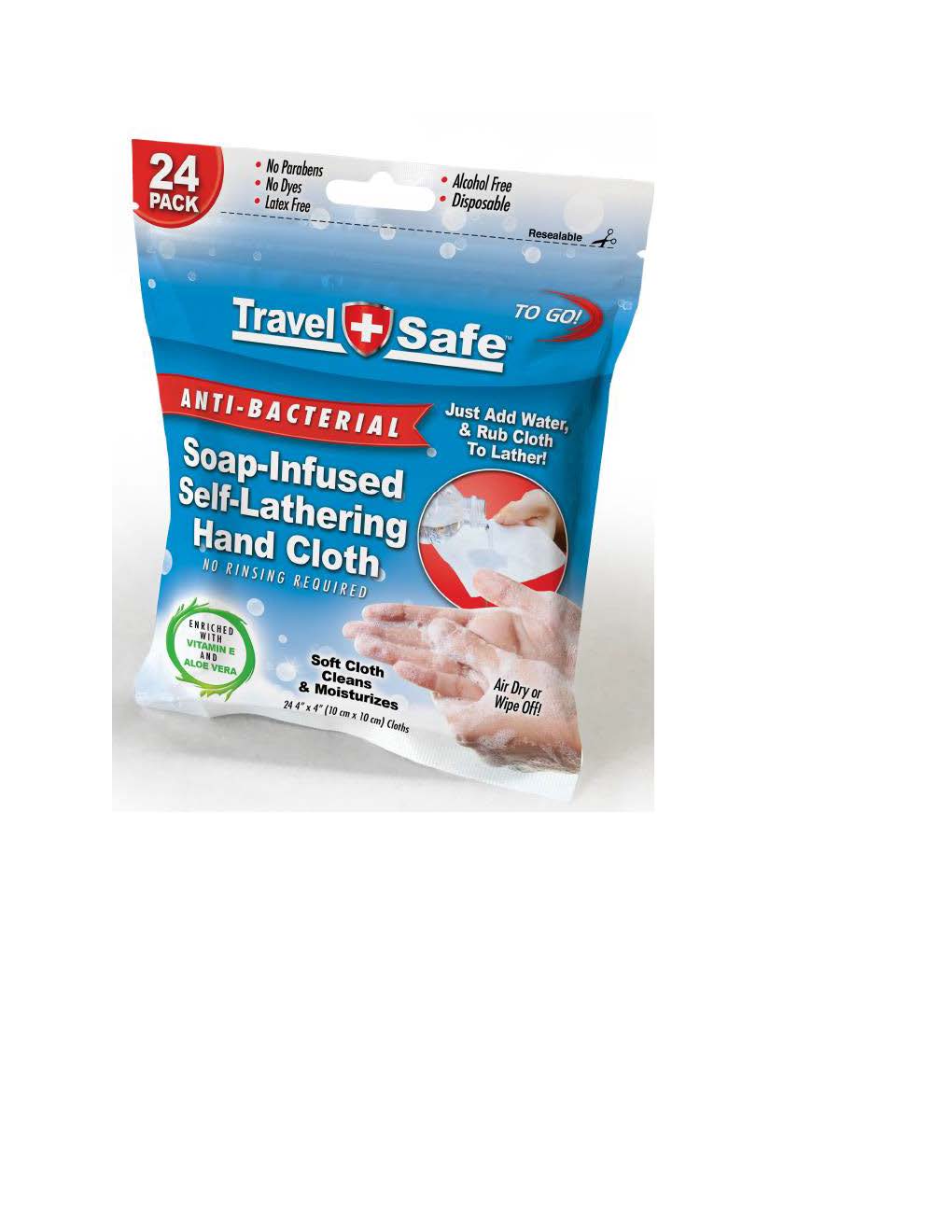 DRUG LABEL: Antibacterial Hand Wipes
NDC: 76749-020 | Form: CLOTH
Manufacturer: Karza Med Group, LLC
Category: otc | Type: HUMAN OTC DRUG LABEL
Date: 20200501

ACTIVE INGREDIENTS: BENZALKONIUM CHLORIDE 0.02 g/0.02 g
INACTIVE INGREDIENTS: POTASSIUM SORBATE; SODIUM LAURYL SULFATE; .ALPHA.-TOCOPHEROL; WATER; SODIUM BENZOATE; SODIUM MYRISTATE; PROPYLENE GLYCOL; COCAMIDOPROPYL BETAINE; SODIUM LAURATE; SODIUM LAURETH SULFATE; SODIUM CHLORIDE

Anti Bacterial Soap

DOSAGE AND ADMINISTRATION

Add Water to Moisten Cloth. Rub Cloth to build Later. Air or Towel Dry

INACTIVE INGREDIENT

Inactive Ingredients: Cocmedyl Propyl Betain, Sodium Lauryl Ether Sulfate, Postassion Sorbate, Sodium Chloride, 1,2 Propendiol, Citric Acid, Sodium Myristate, Sodium Dodcyl Sulfate, Fatty Esther Ethioxylates, Vitamin E, Aloe Vera.

INDICATIONS AND USAGE

For Hand Sanitizing and Decreasing Bacteria on Hands. If irritation occurs stop usage.

Keep out of Reach of Children.

Purpose: Antibacterial

WARNINGS

Warning, For external use Only